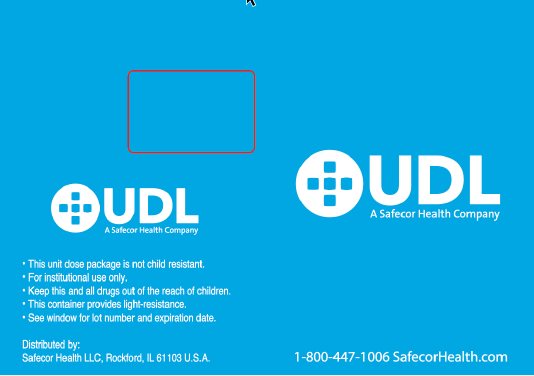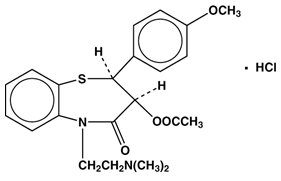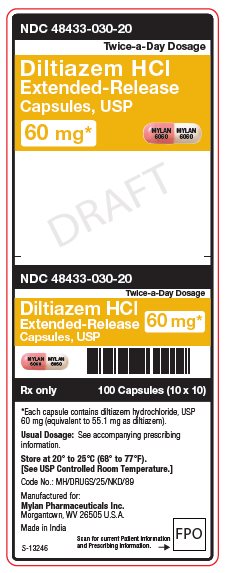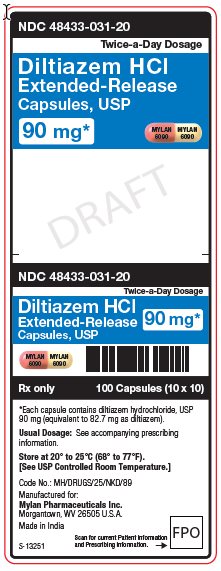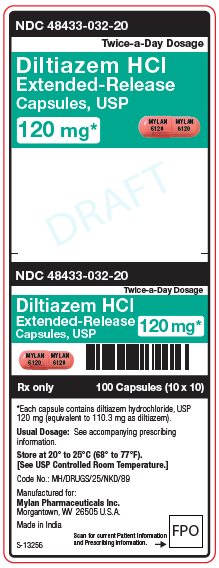 DRUG LABEL: Diltiazem Hydrochloride
NDC: 48433-030 | Form: CAPSULE, EXTENDED RELEASE
Manufacturer: Safecor Health LLC
Category: prescription | Type: HUMAN PRESCRIPTION DRUG LABEL
Date: 20260203

ACTIVE INGREDIENTS: DILTIAZEM HYDROCHLORIDE 60 mg/1 1
INACTIVE INGREDIENTS: DIETHYL PHTHALATE; FD&C RED NO. 40; GELATIN, UNSPECIFIED; HYPROMELLOSE, UNSPECIFIED; MALTODEXTRIN; METHACRYLIC ACID - METHYL METHACRYLATE COPOLYMER (1:2); POLYETHYLENE GLYCOL, UNSPECIFIED; POVIDONE, UNSPECIFIED; SILICON DIOXIDE; SODIUM LAURYL SULFATE; STARCH, CORN; SUCROSE; TITANIUM DIOXIDE; FERROSOFERRIC OXIDE; D&C YELLOW NO. 10; FD&C BLUE NO. 1; FD&C BLUE NO. 2; PROPYLENE GLYCOL; SHELLAC

DESCRIPTION

Diltiazem hydrochloride is a calcium ion cellular influx inhibitor (slow channel blocker or calcium antagonist). Chemically, diltiazem hydrochloride is (+)-5-[2-(Dimethylamino)ethyl]- cis-2,3-dihydro-3-hydroxy-2-(p-methoxyphenyl) -1,5-benzothiazepin-4(5 H)-one acetate (ester) monohydrochloride. The chemical structure is

Diltiazem hydrochloride, USP is a white to off-white crystalline powder with a bitter taste. It is soluble in water, methanol, and chloroform. It has a molecular weight of 450.98. Each diltiazem hydrochloride extended-release capsule, USP contains either 60 mg diltiazem hydrochloride, USP (equivalent to 55.1 mg diltiazem), 90 mg diltiazem hydrochloride, USP (equivalent to 82.7 mg diltiazem), or 120 mg diltiazem hydrochloride, USP (equivalent to 110.3 mg diltiazem).

Inactive ingredients: diethyl phthalate, FD&C Red No. 40, gelatin, hypromellose, maltodextrin, methacrylic acid copolymer Type B, polyethylene glycol, povidone, silicon dioxide, sodium lauryl sulfate, sugar spheres (corn starch and sucrose) and titanium dioxide.

The 90 mg capsules also contain D&C Yellow No. 10.

In addition, the black imprinting ink contains black iron oxide, D&C Yellow No. 10 Aluminum Lake, FD&C Blue No. 1 Aluminum Lake, FD&C Blue No. 2 Aluminum Lake, FD&C Red No. 40 Aluminum Lake, propylene glycol and shellac glaze.

Meets USP Dissolution Test 4.

For oral administration.

CLINICAL PHARMACOLOGY

The therapeutic effects of diltiazem hydrochloride are believed to be related to its ability to inhibit the influx of calcium ions during membrane depolarization of cardiac and vascular smooth muscle.

Mechanism of Action

Diltiazem hydrochloride extended-release capsules produce their antihypertensive effect primarily by relaxation of vascular smooth muscle and the resultant decrease in peripheral vascular resistance. The magnitude of blood pressure reduction is related to the degree of hypertension; thus, hypertensive individuals experience an antihypertensive effect, whereas there is only a modest fall in blood pressure in normotensives.

Hemodynamic and Electrophysiological Effects

Like other calcium channel antagonists, diltiazem decreases sinoatrial and atrioventricular conduction in isolated tissues and has a negative inotropic effect in isolated preparations. In the intact animal, prolongation of the AH interval can be seen at higher doses.

In man, diltiazem prevents spontaneous and ergonovine-provoked coronary artery spasm. It causes a decrease in peripheral vascular resistance and a modest fall in blood pressure in normotensive individuals and, in exercise tolerance studies in patients with ischemic heart disease, reduces the heart rate-blood pressure product for any given workload. Studies to date, primarily in patients with good ventricular function, have not revealed evidence of a negative inotropic effect; cardiac output, ejection fraction, and left ventricular end diastolic pressure have not been affected. Increased heart failure has, however, been reported in occasional patients with preexisting impairment of ventricular function. There are as yet few data on the interaction of diltiazem and beta-blockers in patients with poor ventricular function. Resting heart rate is usually slightly reduced by diltiazem.

Diltiazem hydrochloride extended-release capsules produce antihypertensive effects both in the supine and standing positions. Postural hypotension is infrequently noted upon suddenly assuming an upright position. No reflex tachycardia is associated with the chronic antihypertensive effects. Diltiazem hydrochloride extended-release capsules decrease vascular resistance, increase cardiac output (by increasing stroke volume), and produce a slight decrease or no change in heart rate. During dynamic exercise, increases in diastolic pressure are inhibited, while maximum achievable systolic pressure is usually reduced. Heart rate at maximum exercise does not change or is slightly reduced. Chronic therapy with diltiazem hydrochloride produces no change or an increase in plasma catecholamines. No increased activity of the renin-angiotensin-aldosterone axis has been observed. Diltiazem hydrochloride extended-release capsules antagonize the renal and peripheral effects of angiotensin II. Hypertensive animal models respond to diltiazem with reductions in blood pressure and increased urinary output and natriuresis without a change in urinary sodium/potassium ratio.

Intravenous diltiazem hydrochloride in doses of 20 mg prolongs AH conduction time and AV node functional and effective refractory periods by approximately 20%. In a study involving single oral doses of 300 mg of diltiazem hydrochloride in six normal volunteers, the average maximum PR prolongation was 14% with no instances of greater than first-degree AV block. Diltiazem-associated prolongation of the AH interval is not more pronounced in patients with first-degree heart block. In patients with sick sinus syndrome, diltiazem significantly prolongs sinus cycle length (up to 50% in some cases).

Chronic oral administration of diltiazem hydrochloride in doses of up to 360 mg/day has resulted in small increases in PR interval, and on occasion produces abnormal prolongation (see WARNINGS).

Pharmacokinetics and Metabolism

Diltiazem is well absorbed from the gastrointestinal tract and is subject to an extensive first-pass effect, giving an absolute bioavailability (compared to intravenous administration) of about 40%. Diltiazem hydrochloride undergoes extensive metabolism in which 2% to 4% of the unchanged drug appears in the urine. In vitrobinding studies show diltiazem hydrochloride is 70% to 80% bound to plasma proteins. Competitive in vitroligand binding studies have also shown diltiazem hydrochloride binding is not altered by therapeutic concentrations of digoxin, hydrochlorothiazide, phenylbutazone, propranolol, salicylic acid, or warfarin. The plasma elimination half-life following single or multiple drug administration is approximately 3.0 to 4.5 hours. Desacetyl diltiazem is also present in the plasma at levels of 10% to 20% of the parent drug and is 25% to 50% as potent a coronary vasodilator as diltiazem. Minimum therapeutic plasma levels of diltiazem hydrochloride appear to be in the range of 50 - 200 ng/mL. There is a departure from linearity when dose strengths are increased; the half-life is slightly increased with dose. A study that compared patients with normal hepatic function to patients with cirrhosis found an increase in half-life and a 69% increase in bioavailability in the hepatically impaired patients. A single study in nine patients with severely impaired renal function showed no difference in the pharmacokinetic profile of diltiazem compared to patients with normal renal function.

Diltiazem Hydrochloride Extended-Release Capsules (Twice-a-Day Dosage)

A single 120 mg dose of the capsule results in detectable plasma levels within 2 to 3 hours and peak plasma levels at 6 to 11 hours. The apparent elimination half-life after single or multiple dosing is 5 to 7 hours. A departure from linearity similar to that observed with the diltiazem hydrochloride tablet is observed. As the dose of diltiazem hydrochloride extended-release capsules is increased from a daily dose of 120 mg (60 mg b.i.d.) to 240 mg (120 mg b.i.d.) daily, there is an increase in area-under-the-curve of 2.6 times. When the dose is increased from 240 mg to 360 mg daily, there is an increase in area-under-the-curve of 1.8 times. The average plasma levels of the capsule dosed twice daily at steady-state are equivalent to the tablet dosed four times daily when the same total daily dose is administered.

INDICATIONS AND USAGE

Diltiazem hydrochloride extended-release capsules (Twice-a-Day Dosage) are indicated for the treatment of hypertension. They may be used alone or in combination with other antihypertensive medications, such as diuretics.

CONTRAINDICATIONS

Diltiazem hydrochloride is contraindicated in (1) patients with sick sinus syndrome except in the presence of a functioning ventricular pacemaker, (2) patients with second- or third-degree AV block except in the presence of a functioning ventricular pacemaker, (3) patients with hypotension (less than 90 mm Hg systolic), (4) patients who have demonstrated hypersensitivity to the drug, and (5) patients with acute myocardial infarction and pulmonary congestion documented by X-ray on admission.

WARNINGS

Cardiac Conduction

Diltiazem hydrochloride prolongs AV node refractory periods without significantly prolonging sinus node recovery time, except in patients with sick sinus syndrome. This effect may rarely result in abnormally slow heart rates (particularly in patients with sick sinus syndrome) or second- or third-degree AV block (9 of 2,111 patients or 0.43%). Concomitant use of diltiazem with beta-blockers or digitalis may result in additive effects on cardiac conduction. A patient with Prinzmetal’s angina developed periods of asystole (2 to 5 seconds) after a single dose of 60 mg of diltiazem. (See ADVERSE REACTIONS.)

Congestive Heart Failure

Although diltiazem has a negative inotropic effect in isolated animal tissue preparations, hemodynamic studies in humans with normal ventricular function have not shown a reduction in cardiac index nor consistent negative effects on contractility (dp/dt). An acute study of oral diltiazem in patients with impaired ventricular function (ejection fraction 24% ± 6%) showed improvement in indices of ventricular function without significant decrease in contractile function (dp/dt). Experience with the use of diltiazem hydrochloride in combination with beta-blockers in patients with impaired ventricular function is limited. Caution should be exercised when using this combination.

Hypotension

Decreases in blood pressure associated with diltiazem hydrochloride therapy may occasionally result in symptomatic hypotension.

Acute Hepatic Injury

Mild elevations of transaminases with and without concomitant elevation in alkaline phosphatase and bilirubin have been observed in clinical studies. Such elevations were usually transient and frequently resolved even with continued diltiazem treatment. In rare instances, significant elevations in enzymes such as alkaline phosphatase, LDH, SGOT, SGPT, and other phenomena consistent with acute hepatic injury have been noted. These reactions tended to occur early after therapy initiation (1 to 8 weeks) and have been reversible upon discontinuation of drug therapy. The relationship to diltiazem hydrochloride is uncertain in some cases, but probable in some. (See PRECAUTIONS.)

PRECAUTIONS

General

Diltiazem hydrochloride is extensively metabolized by the liver and excreted by the kidneys and in bile. As with any drug given over prolonged periods, laboratory parameters of renal and hepatic function should be monitored at regular intervals. The drug should be used with caution in patients with impaired renal or hepatic function. In subacute and chronic dog and rat studies designed to produce toxicity, high doses of diltiazem were associated with hepatic damage. In special subacute hepatic studies, oral doses of 125 mg/kg and higher in rats were associated with histological changes in the liver which were reversible when the drug was discontinued. In dogs, doses of 20 mg/kg were also associated with hepatic changes; however, these changes were reversible with continued dosing.

Dermatological events (see ADVERSE REACTIONS) may be transient and may disappear despite continued use of diltiazem hydrochloride. However, skin eruptions progressing to erythema multiforme and/or exfoliative dermatitis have also been infrequently reported. Should a dermatologic reaction persist, the drug should be discontinued.

Drug Interactions

Due to the potential for additive effects, caution and careful titration are warranted in patients receiving diltiazem hydrochloride concomitantly with any agents known to affect cardiac contractility and/or conduction (see WARNINGS). Pharmacologic studies indicate that there may be additive effects in prolonging AV conduction when using beta-blockers or digitalis concomitantly with diltiazem hydrochloride (see WARNINGS).

As with all drugs, care should be exercised when treating patients with multiple medications. Diltiazem is both a substrate and an inhibitor of the cytochrome P-450 3A4 enzyme system. Other drugs that are specific substrates, inhibitors, or inducers of this enzyme system may have a significant impact on the efficacy and side effect profile of diltiazem. Patients taking other drugs that are substrates of CYP450 3A4, especially patients with renal and/or hepatic impairment, may require dosage adjustment when starting or stopping concomitantly administered diltiazem in order to maintain optimum therapeutic blood levels.

Anesthetics

The depression of cardiac contractility, conductivity, and automaticity as well as the vascular dilation associated with anesthetics may be potentiated by calcium channel blockers. When used concomitantly, anesthetics and calcium blockers should be titrated carefully.

Benzodiazepines

Studies showed that diltiazem increased the AUC of midazolam and triazolam by 3- to 4-fold and the Cmaxby 2-fold, compared to placebo. The elimination half-life of midazolam and triazolam also increased (1.5- to 2.5-fold) during coadministration with diltiazem. These pharmacokinetic effects seen during diltiazem coadministration can result in increased clinical effects (e.g., prolonged sedation) of both midazolam and triazolam.

Beta-blockers

Controlled and uncontrolled domestic studies suggest that concomitant use of diltiazem hydrochloride and beta-blockers is usually well tolerated, but available data are not sufficient to predict the effects of concomitant treatment in patients with left ventricular dysfunction or cardiac conduction abnormalities.

Administration of diltiazem hydrochloride concomitantly with propranolol in five normal volunteers resulted in increased propranolol levels in all subjects and bioavailability of propranolol was increased approximately 50%. In vitro, propranolol appears to be displaced from its binding sites by diltiazem. If combination therapy is initiated or withdrawn in conjunction with propranolol, an adjustment in the propranolol dose may be warranted (see WARNINGS).

Buspirone

In nine healthy subjects, diltiazem significantly increased the mean buspirone AUC 5.5-fold and Cmax4.1-fold compared to placebo. The T1/2and Tmaxof buspirone were not significantly affected by diltiazem. Enhanced effects and increased toxicity of buspirone may be possible during concomitant administration with diltiazem. Subsequent dose adjustments may be necessary during coadministration and should be based on clinical assessment.

Carbamazepine

Concomitant administration of diltiazem with carbamazepine has been reported to result in elevated serum levels of carbamazepine (40% to 72% increase), resulting in toxicity in some cases. Patients receiving these drugs concurrently should be monitored for a potential drug interaction.

Cimetidine

A study in six healthy volunteers has shown a significant increase in peak diltiazem plasma levels (58%) and area-under-the-curve (53%) after a 1-week course of cimetidine at 1,200 mg per day and a single dose of diltiazem 60 mg. Ranitidine produced smaller, nonsignificant increases. The effect may be mediated by cimetidine’s known inhibition of hepatic cytochrome P-450, the enzyme system responsible for the first-pass metabolism of diltiazem. Patients currently receiving diltiazem therapy should be carefully monitored for a change in pharmacological effect when initiating and discontinuing therapy with cimetidine. An adjustment in the diltiazem dose may be warranted.

Clonidine

Sinus bradycardia resulting in hospitalization and pacemaker insertion has been reported in association with the use of clonidine concurrently with diltiazem. Monitor heart rate in patients receiving concomitant diltiazem and clonidine.

Cyclosporine

A pharmacokinetic interaction between diltiazem and cyclosporine has been observed during studies involving renal and cardiac transplant patients. In renal and cardiac transplant recipients, a reduction of cyclosporine dose ranging from 15% to 48% was necessary to maintain cyclosporine trough concentrations similar to those seen prior to the addition of diltiazem. If these agents are to be administered concurrently, cyclosporine concentrations should be monitored, especially when diltiazem therapy is initiated, adjusted or discontinued. The effect of cyclosporine on diltiazem plasma concentrations has not been evaluated.

Digitalis

Administration of diltiazem hydrochloride with digoxin in 24 healthy male subjects increased plasma digoxin concentrations approximately 20%. Another investigator found no increase in digoxin levels in 12 patients with coronary artery disease. Since there have been conflicting results regarding the effect of digoxin levels, it is recommended that digoxin levels be monitored when initiating, adjusting, and discontinuing diltiazem hydrochloride therapy to avoid possible over- or under-digitalization (see WARNINGS).

Ivabradine

Concurrent use of diltiazem increases exposure to ivabradine and may exacerbate bradycardia and conduction disturbances. Avoid concomitant use of ivabradine and diltiazem.

Quinidine

Diltiazem significantly increases the AUC(0 →∞)of quinidine by 51%, T1/2by 36%, and decreases its CLoralby 33%. Monitoring for quinidine adverse effects may be warranted and the dose adjusted accordingly.

Rifampin

Coadministration of rifampin with diltiazem lowered the diltiazem plasma concentrations to undetectable levels. Coadministration of diltiazem with rifampin or any known CYP3A4 inducer should be avoided when possible, and alternative therapy considered.

Statins

Diltiazem is an inhibitor of CYP3A4 and has been shown to increase significantly the AUC of some statins. The risk of myopathy and rhabdomyolysis with statins metabolized by CYP3A4 may be increased with concomitant use of diltiazem. When possible, use a non-CYP3A4-metabolized statin together with diltiazem; otherwise, dose adjustments for both diltiazem and the statin should be considered along with close monitoring for signs and symptoms of any statin related adverse events.

In a healthy volunteer cross-over study (N = 10), coadministration of a single 20 mg dose of simvastatin at the end of a 14 day regimen with 120 mg BID diltiazem extended-release resulted in a 5-fold increase in mean simvastatin AUC versus simvastatin alone. Subjects with increased average steady-state exposures of diltiazem showed a greater fold increase in simvastatin exposure. Computer-based simulations showed that at a daily dose of 480 mg of diltiazem, an 8- to 9-fold mean increase in simvastatin AUC can be expected. If coadministration of simvastatin with diltiazem is required, limit the daily doses of simvastatin to 10 mg and diltiazem to 240 mg.

In a ten-subject randomized, open label, 4-way cross over study, co-administration of diltiazem (120 mg bid, diltiazem SR for 2 weeks) with single 20 mg dose of lovastatin resulted in 3- to 4- fold increase in mean lovastatin AUC and Cmaxversus lovastatin alone. In the same study, there was no significant change in 20 mg single dose pravastatin AUC and Cmaxduring diltiazem co-administration. Diltiazem plasma levels were not significantly affected by lovastatin or pravastatin.

Carcinogenesis, Mutagenesis, Impairment of Fertility

A 24-month study in rats and a 21-month study in mice showed no evidence of carcinogenicity. There was also no mutagenic response in in vitrobacterial tests. No intrinsic effect on fertility was observed in rats.

Pregnancy

Reproduction studies have been conducted in mice, rats, and rabbits. Administration of doses ranging from five to ten times greater (on a mg/kg basis) than the daily recommended therapeutic dose has resulted in embryo and fetal lethality. These doses, in some studies, have been reported to cause skeletal abnormalities. In the perinatal/postnatal studies, there was some reduction in early individual pup weights and survival rates. There was an increased incidence of stillbirths at doses of 20 times the human dose or greater.

There are no well controlled studies in pregnant women; therefore, use diltiazem hydrochloride in pregnant women only if the potential benefit justifies the potential risk to the fetus.

Nursing Mothers

Diltiazem is excreted in human milk. One report suggests that concentrations in breast milk may approximate serum levels. If use of diltiazem hydrochloride is deemed essential, an alternative method of infant feeding should be instituted.

Pediatric Use

Safety and effectiveness in pediatric patients have not been established.

Geriatric Use

Clinical studies of diltiazem did not include sufficient numbers of subjects aged 65 and over to determine whether they respond differently from younger subjects. Other reported clinical experience has not identified differences in responses between the elderly and younger patients. In general, dose selection for an elderly patient should be cautious, usually starting at the low end of the dosing range, reflecting the greater frequency of decreased hepatic, renal, or cardiac function, and of concomitant disease or other drug therapy.

ADVERSE REACTIONS

Serious adverse reactions have been rare in studies carried out to date, but it should be recognized that patients with impaired ventricular function and cardiac conduction abnormalities have usually been excluded from these studies.

The adverse events described below represent events observed in clinical studies of hypertensive patients receiving either diltiazem hydrochloride tablets or diltiazem hydrochloride extended-release capsules, as well as experiences observed in studies of angina and during marketing. The most common events in hypertension studies are shown in a table with rates in placebo patients shown for comparison. Less common events are listed by body system; these include any adverse reactions seen in angina studies that were not observed in hypertension studies. In all hypertensive patients studied (over 900), the most common adverse events were edema (9%), headache (8%), dizziness (6%), asthenia (5%), sinus bradycardia (3%), flushing (3%), and first-degree AV block (3%). Only edema and perhaps bradycardia and dizziness were dose related. The most common events observed in clinical studies (over 2,100 patients) of angina patients and hypertensive patients receiving diltiazem hydrochloride tablets or diltiazem hydrochloride extended-release capsules were (i.e., greater than 1%) edema (5.4%), headache (4.5%), dizziness (3.4%), asthenia (2.8%), first-degree AV block (1.8%), flushing (1.7%), nausea (1.6%), bradycardia (1.5%), and rash (1.5%).

Double Blind Placebo Controlled Hypertension Trials
Adverse | Diltiazem; N = 315; No. pts (%) | Placebo; N = 211; No. pts (%)
Headache | 38 (12%) | 17 (8%)
AV block first degree | 24 (7.6%) | 4 (1.9%)
Dizziness | 22 (7%) | 6 (2.8%)
Edema | 19 (6%) | 2 (0.9%)
Bradycardia | 19 (6%) | 3 (1.4%)
ECG abnormality | 13 (4.1%) | 3 (1.4%)
Asthenia | 10 (3.2%) | 1 (0.5%)
Constipation | 5 (1.6%) | 2 (0.9%)
Dyspepsia | 4 (1.3%) | 1 (0.5%)
Nausea | 4 (1.3%) | 2 (0.9%)
Palpitations | 4 (1.3%) | 2 (0.9%)
Polyuria | 4 (1.3%) | 2 (0.9%)
Somnolence | 4 (1.3%) | —
Alk phos increase | 3 (1%) | 1 (0.5%)
Hypotension | 3 (1%) | 1 (0.5%)
Insomnia | 3 (1%) | 1 (0.5%)
Rash | 3 (1%) | 1 (0.5%)
AV block second degree | 2 (0.6%) | —

In addition, the following events were reported infrequently (less than 1%) with diltiazem hydrochloride extended-release capsules or diltiazem hydrochloride tablets or have been observed in angina or hypertension trials.

Cardiovascular: Angina, arrhythmia, second- or third-degree AV block (see Conduction Warning), bundle branch block, congestive heart failure, syncope, tachycardia, ventricular extrasystoles.

Nervous System: Abnormal dreams, amnesia, depression, gait abnormality, hallucinations, nervousness, paresthesia, personality change, tremor.

Gastrointestinal: Anorexia, diarrhea, dry mouth, dysgeusia, mild elevations of SGOT, SGPT, and LDH (see Hepatic Warnings), thirst, vomiting, weight increase.

Dermatological: Petechiae, photosensitivity, pruritus, urticaria.

Other: Amblyopia, CPK increase, dyspnea, epistaxis, eye irritation, hyperglycemia, hyperuricemia, impotence, muscle cramps, nasal congestion, nocturia, osteoarticular pain, sexual difficulties, tinnitus.

The following post-marketing events have been reported infrequently in patients receiving diltiazem hydrochloride: acute generalized exanthematous pustulosis, allergic reactions, alopecia, angioedema (including facial or periorbital edema), asystole, erythema multiforme (including Stevens-Johnson Syndrome, toxic epidermal necrolysis), extrapyramidal symptoms, gingival hyperplasia, hemolytic anemia, increased bleeding time, leukopenia, photosensitivity (including lichenoid keratosis and hyperpigmentation at sun-exposed skin areas), purpura, retinopathy, myopathy, and thrombocytopenia. There have been observed cases of a generalized rash, some characterized as leukocytoclastic vasculitis. In addition, events such as myocardial infarction have been observed which are not readily distinguishable from the natural history of the disease in these patients. A definitive cause and effect relationship between these events and diltiazem hydrochloride therapy cannot yet be established. Exfoliative dermatitis (proven by rechallenge) has also been reported.

OVERDOSAGE

The oral LD50’s in mice and rats range from 415 to 740 mg/kg and from 560 to 810 mg/kg, respectively. The intravenous LD50’s in these species were 60 and 38 mg/kg, respectively. The oral LD50in dogs is considered to be in excess of 50 mg/kg, while lethality was seen in monkeys at 360 mg/kg.

The toxic dose in man is not known. Due to extensive metabolism, blood levels after a standard dose of diltiazem can vary over tenfold, limiting the usefulness of blood levels in overdose cases.

There have been reports of diltiazem overdose in doses ranging from 1 g to 18 g. Of cases with known outcome, most patients recovered and in cases with a fatal outcome, the majority involved multiple drug ingestion.

Events observed following diltiazem overdose included bradycardia, hypotension, heart block, and cardiac failure. Most reports of overdose described some supportive medical measure and/or drug treatment. Bradycardia frequently responded favorably to atropine, as did heart block, although cardiac pacing was also frequently utilized to treat heart block. Fluids and vasopressors were used to maintain blood pressure and in cases of cardiac failure inotropic agents were administered. In addition, some patients received treatment with ventilatory support, gastric lavage, activated charcoal, and/or intravenous calcium.

The effectiveness of intravenous calcium administration to reverse the pharmacological effects of diltiazem overdose has been inconsistent. In a few reported cases, overdose with calcium channel blockers associated with hypotension and bradycardia that was initially refractory to atropine became more responsive to atropine after the patients received intravenous calcium. In some cases, intravenous calcium has been administered (1 g calcium chloride or 3 g calcium gluconate) over 5 minutes and repeated every 10-20 minutes as necessary. Calcium gluconate has also been administered as a continuous infusion at a rate of 2 g per hour for 10 hours. Infusions of calcium for 24 hours or more may be required. Patients should be monitored for signs of hypercalcemia.

In the event of overdosage or exaggerated response, appropriate supportive measures should be employed in addition to gastrointestinal decontamination. Diltiazem does not appear to be removed by peritoneal or hemodialysis. Limited data suggest that plasmapheresis or charcoal hemoperfusion may hasten diltiazem elimination following overdose. Based on the known pharmacological effects of diltiazem and/or reported clinical experiences the following measures may be considered:

Bradycardia

Administer atropine (0.6 to 1 mg). If there is no response to vagal blockade, administer isoproterenol cautiously.

High-Degree AV Block

Treat as for bradycardia above. Fixed high degree AV block should be treated with cardiac pacing.

Cardiac Failure

Administer inotropic agents (isoproterenol, dopamine, or dobutamine) and diuretics.

Hypotension

Vasopressors (e.g., dopamine or norepinephrine bitartrate).

Actual treatment and dosage should depend on the severity of the clinical situation and the judgment and experience of the treating physician.

DOSAGE AND ADMINISTRATION

Dosages must be adjusted to each patient’s needs, starting with 60 to 120 mg twice daily. Maximum antihypertensive effect is usually observed by 14 days of chronic therapy; therefore, dosage adjustments should be scheduled accordingly. Although individual patients may respond to lower doses, the usual optimum dosage range in clinical trials was 240 to 360 mg/day.

Diltiazem hydrochloride extended-release capsules have an additive antihypertensive effect when used with other antihypertensive agents. Therefore, the dosage of diltiazem hydrochloride extended-release capsules or the concomitant antihypertensives may need to be adjusted when adding one to the other. See WARNINGSand PRECAUTIONSregarding use with beta-blockers.

HOW SUPPLIED:

Diltiazem Hydrochloride Extended-Release Capsules, USP (Twice-a-Day Dosage) are available containing either 60 mg diltiazem hydrochloride, USP (equivalent to 55.1 mg diltiazem), 90 mg diltiazem hydrochloride, USP (equivalent to 82.7 mg diltiazem), or 120 mg diltiazem hydrochloride, USP (equivalent to 110.3 mg diltiazem).

The 60 mg capsules are hard-shell gelatin capsules with a coral opaque cap and white opaque body filled with white to off-white beads. The capsules are axially printed with MYLANover 6060in black ink on the cap and body. They are available as follows:

NDC 48433-030-20 – Unit dose blister packages of 100 (10 cards of 10 capsules each).

The 90 mg capsules are hard-shell gelatin capsules with a coral opaque cap and ivory opaque body filled with white to off-white beads. The capsules are axially printed with MYLANover 6090in black ink on the cap and body. They are available as follows:

NDC 48433-031-20 – Unit dose blister packages of 100 (10 cards of 10 capsules each).

The 120 mg capsules are hard-shell gelatin capsules with a coral opaque cap and coral opaque body filled with white to off-white beads. The capsules are axially printed with MYLANover 6120in black ink on the cap and body. They are available as follows:

NDC 48433-032-20 – Unit dose blister packages of 100 (10 cards of 10 capsules each).

Store at 20º to 25ºC (68º to 77ºF). [See USP Controlled Room Temperature.]
Avoid excessive humidity.

Manufactured for:
Mylan Pharmaceuticals Inc.
Morgantown, WV 26505 U.S.A.

Manufactured by:
Mylan Laboratories Limited
Hyderabad — 500 096, India

Distributed by:
Safecor Health LLC
Rockford, IL 61103 U.S.A.

75106328

Revised: 9/2024
MX:DILER:R3

PRINCIPAL DISPLAY PANEL – 60 mg

NDC 48433-030-20

Twice-a-Day Dosage

Diltiazem HCl
Extended-Release
Capsules, USP
60 mg*

100 Capsules (10 x 10)

*Each capsule contains
diltiazem hydrochloride, USP 60 mg
(equivalent to 55.1 mg as diltiazem).

Usual Dosage:See accompanying
prescribing information.

Store at 20° to 25°C (68° to 77°F). [See
USP Controlled Room Temperature.]

Code No.: MH/DRUGS/25/NKD/89

Manufactured for:
Mylan Pharmaceuticals Inc.
Morgantown, WV 26505 U.S.A.

Made in India

Rx only

S-13246

Distributed by:

Safecor Health LLC

Rockford, IL 61103 U.S.A.

This unit dose package is not child resistant.

For institutional use only.

Keep this and all drugs out of the reach of children.

This container provides light-resistance.

See window for lot number and expiration date.

PRINCIPAL DISPLAY PANEL – 90 mg

NDC 48433-031-20

Twice-a-Day Dosage

Diltiazem HCl
Extended-Release
Capsules, USP
90 mg*

100 Capsules (10 x 10)

*Each capsule contains diltiazem
hydrochloride, USP 90 mg
(equivalent to 82.7 mg as diltiazem).

Usual Dosage:See accompanying
prescribing information.

Store at 20° to 25°C (68° to 77°F). [See
USP Controlled Room Temperature.]

Code No.: MH/DRUGS/25/NKD/89

Manufactured for:
Mylan Pharmaceuticals Inc.
Morgantown, WV 26505 U.S.A.

Made in India

Rx only

S-Distributed by:

Safecor Health LLC

Rockford, IL 61103 U.S.A.

This unit dose package is not child resistant.

For institutional use only.

Keep this and all drugs out of the reach of children.

This container provides light-resistance.

See window for lot number and expiration date.

PRINCIPAL DISPLAY PANEL – 120 mg

NDC 48433-032-20

Twice-a-Day Dosage

Diltiazem HCl
Extended-Release
Capsules, USP
120 mg*

100 Capsules (10 x 10)

*Each capsule contains diltiazem
hydrochloride, USP 120 mg
(equivalent to 110.3 mg as diltiazem).

Usual Dosage:See accompanying
prescribing information.

Store at 20° to 25°C (68° to 77°F). [See
USP Controlled Room Temperature.]

Code No.: MH/DRUGS/25/NKD/89

Manufactured for:
Mylan Pharmaceuticals Inc.
Morgantown, WV 26505 U.S.A.

Made in India

Rx only

S-13256

Distributed by:

Safecor Health LLC

Rockford, IL 61103 U.S.A.

This unit dose package is not child resistant.

For institutional use only.

Keep this and all drugs out of the reach of children.

This container provides light-resistance.

See window for lot number and expiration date.